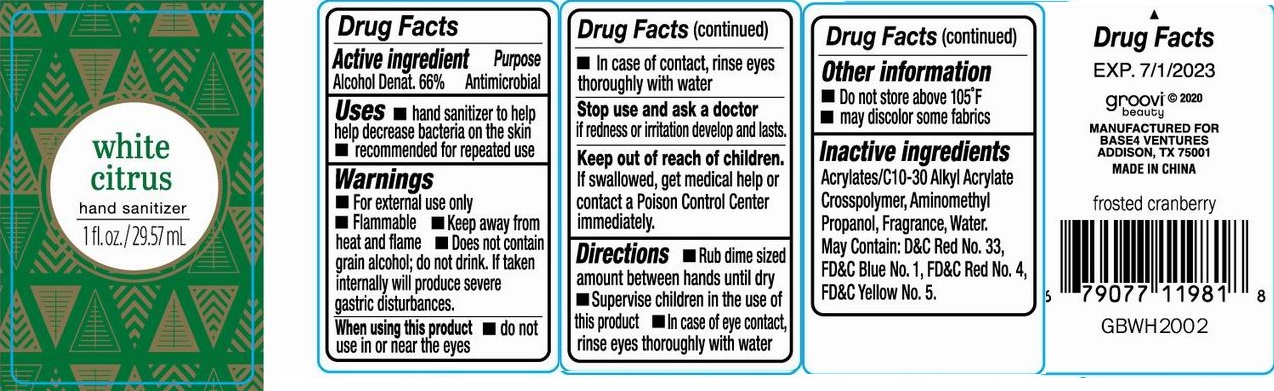 DRUG LABEL: White Citrus Hand Sanitizer
NDC: 56136-347 | Form: GEL
Manufacturer: Ganzhou Olivee Cosmetic Co., Ltd.
Category: otc | Type: HUMAN OTC DRUG LABEL
Date: 20200627

ACTIVE INGREDIENTS: ALCOHOL 66 mL/100 mL
INACTIVE INGREDIENTS: WATER; CARBOMER COPOLYMER TYPE A; AMINOMETHYLPROPANOL

HAND SANITIZER

Active ingredient

Alcohol Denat. 66%

Purpose

Antimicrobial

Use

- hand sanitizer to help Decreases bacteria on the skin
- recommended for repeated use

Warnings

For external use only.

Flammable. Keep product away from heat or flame.

Does not contain grain alcohol; do not drink, if taken internally will produce severe gastric disturbances.

When using this product Do not use in or near the eyes. In case of contact, rinse eyes thoroughly with water.

Stop use and ask a doctor if irritation or redness develops and lasts.

Other information

- Do not store above 105℉
- May discolor some fabrics

Keep out of reach of children.

If swallowed, get medical help or contact a Poison Control Center right away.

Directions

- Rub dime sized amount between hands until dry
- Supervise children in the use of this product
- In case of eye contact, rinse eyes thoroughly with water

Inactive ingredients

Water, Fragrance, Acrylates/C10-30 Alkyl Acrylate Crosspolymer, Aminomethyl Propanol. May contain: D&C Red No. 33, FD&C Red No. 4, FD&C Yellow No. 5, FD&C Blue No. 1.